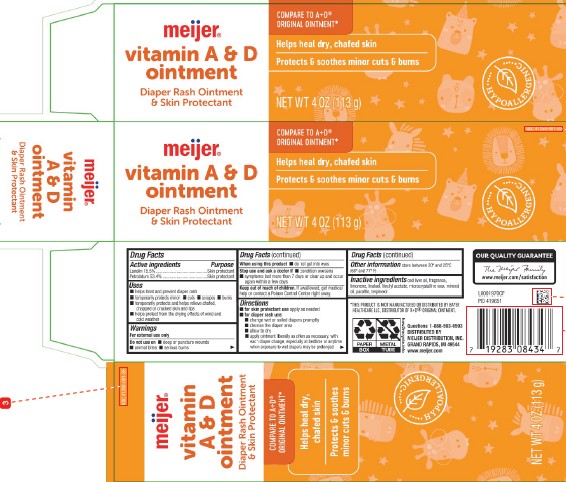 DRUG LABEL: Vitamin A D
NDC: 41250-091 | Form: OINTMENT
Manufacturer: Meijer, Inc.
Category: otc | Type: HUMAN OTC DRUG LABEL
Date: 20260219

ACTIVE INGREDIENTS: LANOLIN 155 mg/1 g; PETROLATUM 534 mg/1 g
INACTIVE INGREDIENTS: COD LIVER OIL; LIMONENE, (+)-; LINALOOL, (+/-)-; LINALYL ACETATE; MICROCRYSTALLINE WAX; MINERAL OIL; PARAFFIN; TERPINEOL

Meijer 013.001/013AC
Vitamin A&D Diaper Rash Ointment

Active ingredients

Lanolin 15.5%

Petrolatum 53.4%

Purpose

Skin protectant

Uses

- helps treat and prevent diaper rash
- temporarily protects minor: cuts - scrapes - burns
- temporarily protects and helps relieve chafed, chapped or cracked skin and lips
- helps protect from the drying effects of wind and cold weather

Warnings

For external use only

Do not use on

- deep or puncture wounds
- animal bites
- serious burns

When using this product

- do not get into eyes

Stop use and ask a doctor if

- condition worsens
- symptoms last more than 7 days or clear up and occur again within a few days

Keep out of reach of children.

If swallowed, get medical help or contact a Poison Control Center right away.

Directions

- for skin protectant use: apply as needed
- for diaper rash use:
- change wet or soiled diapers promptly
- cleanse the diaper area and allow to dry
- apply ointment liberally as often as necessary, with each diaper change, especially at bedtime or anytime when exposure to wet diapers may be prolonged

Other information

store between 20º and 25ºC (68º and 77ºF)

Inactive ingredients

cod liver oil, fragrance, limonene, linalool, linalyl acetate, microcrystalline wax, mineral oil, paraffin, terpineol

Disclaimer

*This product is not manufactured or distributed by Bayer Healthcare LLC, distributor of A+D®Original Ointment.

Adverse Reactions

OUR QUALITY GUARANTEE

The Meijer Family

www.meijer.com/satisfaction

Questions? 1-888-593-0593

DISTRIBUTED BY MEIJER DISTRIBUTION, INC.

GRAND RAPIDS, MI 49544

www.meijer.com

PAPER BOX

METAL TUBE

how2recycle.info

Principal Display Panel

NDC 41250-091-26

meijer®

Compare to A+D®Original Ointment*

vitamin A & D ointment

Diaper Rash Ointment & Skin Protectant

Helps heal dry, chafed skin

Protects & soothes minor cuts & burns

HYPOALLERGENIC

NET WT. 4 OZ (113 g)